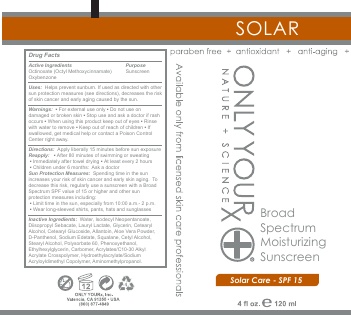 DRUG LABEL: Broad Spectrum Moisturizing Sunscreen-SPF 15, Octinoxate, Oxybenzone
NDC: 70367-006 | Form: LOTION
Manufacturer: Only Yourx, Inc.
Category: otc | Type: HUMAN OTC DRUG LABEL
Date: 20200123

ACTIVE INGREDIENTS: OCTINOXATE 6.3 g/100 mL; OXYBENZONE 2.7 g/100 mL
INACTIVE INGREDIENTS: CETYL ALCOHOL; STEARYL ALCOHOL; ETHYLHEXYLGLYCERIN; ISODECYL NEOPENTANOATE; SQUALANE; ALOE VERA LEAF; PANTHENOL; POLYSORBATE 60; PHENOXYETHANOL; (C10-C30)ALKYL METHACRYLATE ESTER; AMINOMETHYLPROPANOL; DIISOPROPYL SEBACATE; LAURYL LACTATE; GLYCERIN; CETEARYL ETHYLHEXANOATE; CETEARYL GLUCOSIDE; ALLANTOIN

Active Ingredients: Octinoxate (Octyl Methoxycinnamate), Oxybenzone

INACTIVE INGREDIENT

Other Ingredients: Water, Isodecyl Neopentanoate, Diisopropyl Sebacate, Lauryl Lactate, Glycerin, Cetearyl Alcohol, Cetearyl Glucoside, Allantoin, Aloe Vera Powder, D-Panthenol, Sodium Edetate, Squalane, Cetyl Alcohol, Stearyl Alcohol, Polysorbate 60, Phenoxyethanol, Ethylhexylglycerin, Carbomer, Acrylates/C10-30 Alkyl Acrylate Crosspolymer, Hydroethylacrylate/Sodium Acryloyldimethyl Copolymer, Aminomethylpropanol

DOSAGE AND ADMINISTRATION

USE INSTRUCTIONS: Apply a liberal amount aproximately 30 minutes prior to sun exposure. For continuous protection, reapply regularly and after swimming and/or exercising

INDICATIONS AND USAGE

Broad spectrum UVA and UVB protection. Lightweight lotion suitable for even oily skin helps to protect damaging rays, moisture loss and premature aging of the skin

PURPOSE

Broad spectrum UVA and UVB protection

Keep Out of Reach of Children. If swallowed, get medical help or contact a Poison Control Center immediately.

WARNINGS

Warnings: For external use only; Do not use on damaged or broken skin; Stop use and ask a doctor if rash occurs; When using this product keep out of eyes; Rinse with water to remove